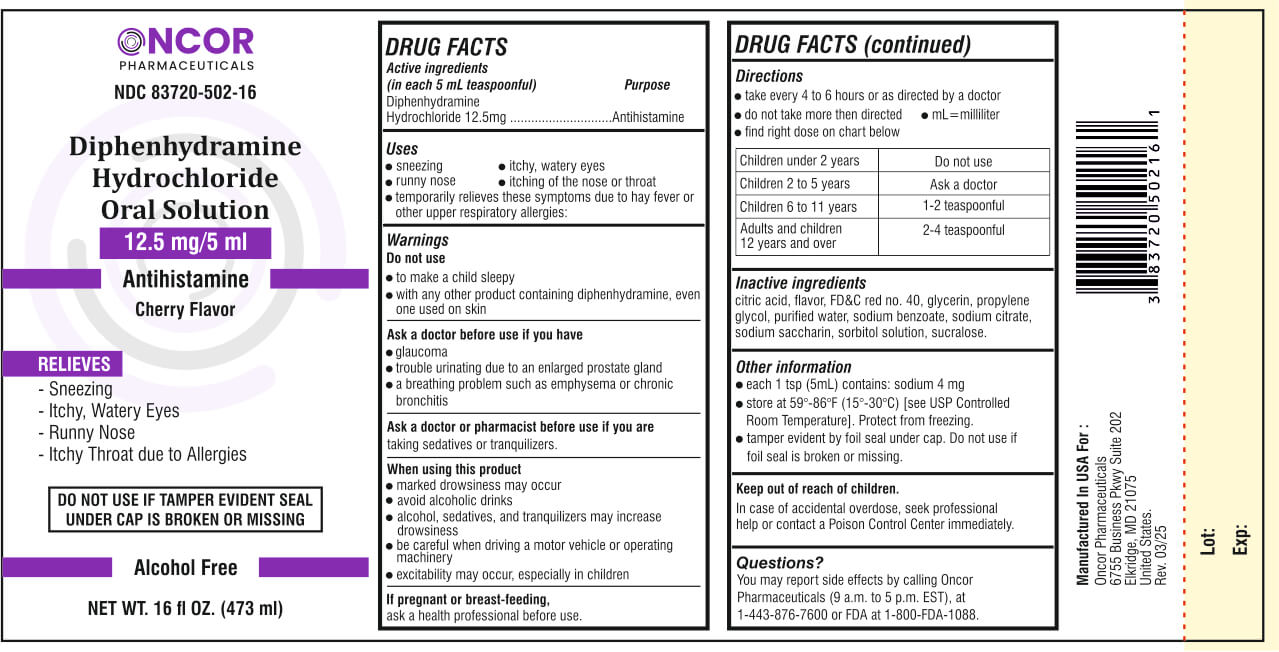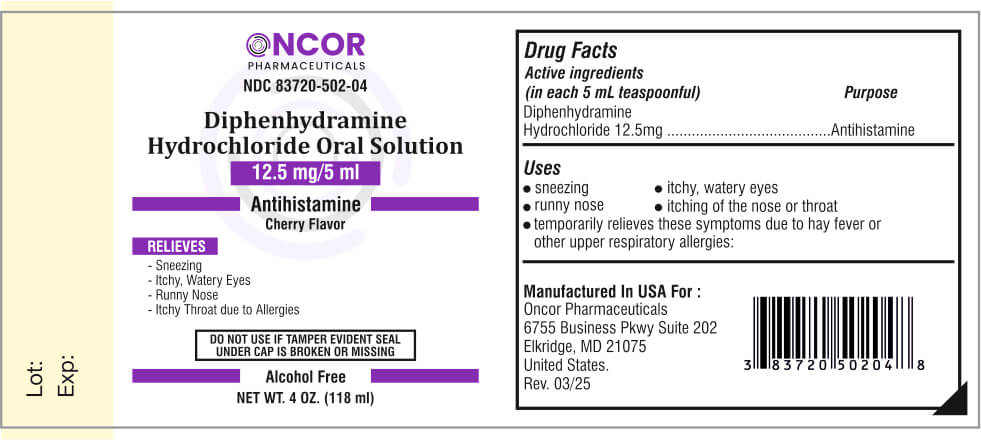 DRUG LABEL: Diphenhydramine Hydrochloride
NDC: 83720-502 | Form: SOLUTION
Manufacturer: Oncor Pharmaceuticals
Category: otc | Type: HUMAN OTC DRUG LABEL
Date: 20250327

ACTIVE INGREDIENTS: DIPHENHYDRAMINE HYDROCHLORIDE 12.5 mg/5 mL
INACTIVE INGREDIENTS: CITRIC ACID; CHERRY; FD&C RED NO. 40; GLYCERIN; PROPYLENE GLYCOL; WATER; SODIUM BENZOATE; SODIUM CITRATE; SODIUM SACCHARIN; SORBITOL SOLUTION; SUCRALOSE

Diphenhydramine Hydrochloride Solution

Active ingredients (in each 5 mL teaspoonful) Purpose

Diphenhydramine Hydrochloride 12.5mg .............................Antihistamine

Uses

- sneezing

- runny nose

- itchy, watery eyes

- itching of the nose or throat

- temporarily relieves these symptoms due to hay fever or other upper respiratory allergies:

Warnings

Do not use

- to make a child sleepy

- with any other product containing diphenhydramine, even one used on skin

Ask a doctor before use if you have

- glaucoma

- trouble urinating due to an enlarged prostate gland

- a breathing problem such as emphysema or chronic bronchitis

Ask a doctor or pharmacist before use if you are

taking sedatives or tranquilizers.

When using this product

- marked drowsiness may occur

- avoid alcoholic drinks

- alcohol, sedatives, and tranquilizers may increase drowsiness

- be careful when driving a motor vehicle or operating machinery

- excitability may occur, especially in children

If pregnant or breast-feeding,

ask a health professional before use.

Directions

- take every 4 to 6 hours or as directed by a doctor

- do not take more then directed

- mL=milliliter

- find right dose on chart below

Children under 2 years | Do not use
Children 2 to 5 years | Ask a doctor
Children 6 to 11 years | 1-2 teaspoonful
Adults and children 12 years and over | 2-4 teaspoonful

Inactive ingredients

citric acid, flavor, FD&C red no. 40, glycerin, propylene glycol, purified water, sodium benzoate, sodium citrate, sodium saccharin, sorbitol solution, sucralose.

Other information

- each 1 tsp (5mL) contains: sodium 4 mg

- store at 59°-86°F (15°-30°C) [see USP Controlled Room Temperature]. Protect from freezing.

- tamper evident by foil seal under cap. Do not use if foil seal is broken or missing.

Keep out of reach of children.

OVERDOSAGE

In case of accidental overdose, seek professional help or contact a Poison Control Center immediately.

Questions?

You may report side effects by calling Oncor Pharmaceuticals (9 a.m. to 5 p.m. EST), at 1-443-876-7600 or FDA at 1-800-FDA-1088.

Principal Display Panel

Oncor Pharmaceuticals

NDC 83720-502-16

Diphenhydramine Hydrochloride
Oral Solution

12.5 mg/5 ml

Antihistamine

Cherry Flavor

RELIEVES

- Sneezing

- Itchy, Watery Eyes

- Runny Nose

- Itchy Throat due to Allergies

DO NOT USE IF TAMPER EVIDENT SEAL
UNDER CAP IS BROKEN OR MISSING

Alcohol Free

NET WT. 16 OZ. (473 ml)

NDC 83720-502-04

Diphenhydramine Hydrochloride
Oral Solution

12.5 mg/5 ml

Antihistamine

Cherry Flavor

RELIEVES

- Sneezing

- Itchy, Watery Eyes

- Runny Nose

- Itchy Throat due to Allergies

DO NOT USE IF TAMPER EVIDENT SEAL
UNDER CAP IS BROKEN OR MISSING

Alcohol Free

NET WT. 4 OZ. (118 ml)

Manufactured In USA For :

Oncor Pharmaceuticals
6755 Business Pkwy Suite 202
Elkridge, MD 21075
United States.
Rev. 03/25